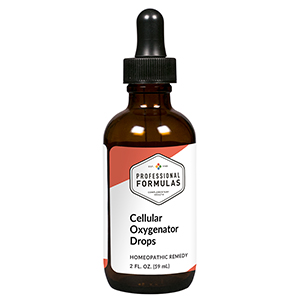 DRUG LABEL: Cellular Oxygenator Drops
NDC: 63083-2095 | Form: LIQUID
Manufacturer: Professional Complementary Health Formulas
Category: homeopathic | Type: HUMAN OTC DRUG LABEL
Date: 20190815

ACTIVE INGREDIENTS: SELENICEREUS GRANDIFLORUS STEM 3 [hp_X]/59 mL; ALPHA LIPOIC ACID 6 [hp_X]/59 mL; MAGNESIUM GLUCONATE 6 [hp_X]/59 mL; MAGNESIUM PHOSPHATE, DIBASIC TRIHYDRATE 6 [hp_X]/59 mL; NIACINAMIDE 6 [hp_X]/59 mL; THIAMINE 6 [hp_X]/59 mL; RIBOFLAVIN 6 [hp_X]/59 mL; PYRIDOXINE 6 [hp_X]/59 mL; ASCORBIC ACID 6 [hp_X]/59 mL; NAJA NAJA VENOM 8 [hp_X]/59 mL; ADENOSINE TRIPHOSPHATE 12 [hp_X]/59 mL; ANTHRAQUINONE 12 [hp_X]/59 mL; COENZYME A 12 [hp_X]/59 mL; NADIDE 12 [hp_X]/59 mL; QUINONE 12 [hp_X]/59 mL
INACTIVE INGREDIENTS: ALCOHOL; WATER

C95

ACTIVE INGREDIENTS

Cactus grandiflorus 3X
Alpha lipoicum acidum 6X
Magnesia gluconicum 6X
Magnesia phosphorica 6X
Nicotinamidum 6X
Vitamin B1 6X
Vitamin B2 6X
Vitamin B6 6X
Vitamin C 6X
Naja tripudians 8X, 12X
Adenosine triphosphate 12X
Anthraquinone 12X
Coenzyme A 12X
Nadidum 12X
Para benzoquinone 12X

QUESTIONS

Professional Formulas

PO Box 2034 Lake Oswego, OR 97035

INDICATIONS

For the temporary relief of fatigue, weakened memory or fogginess, minor muscle or joint pain, or occasional headaches.*

PURPOSE

*Claims based on traditional homeopathic practice, not accepted medical evidence. Not FDA evaluated.

WARNINGS

In case of overdose, get medical help or contact a poison control center right away.

Keep out of the reach of children.

PREGNANCY OR BREAST FEEDING

If pregnant or breastfeeding, ask a healthcare professional before use.

DIRECTIONS

Place drops under tongue 30 minutes before/after meals. Adults and children 12 years and over: Take 10 drops up to 3 times per day. Consult a physician for use in children under 12 years of age.

OTHER INFORMATION

Tamper resistant. If seal is broken, do not use. After opening, close container tightly and store at room temperature away from heat.

INACTIVE INGREDIENTS

20% ethanol, purified water.

LABEL

Est 1985

Professional Formulas

Complementary Health

Cellular Oxygenator Drops

Homeopathic Remedy

2 FL. OZ. (59 mL)